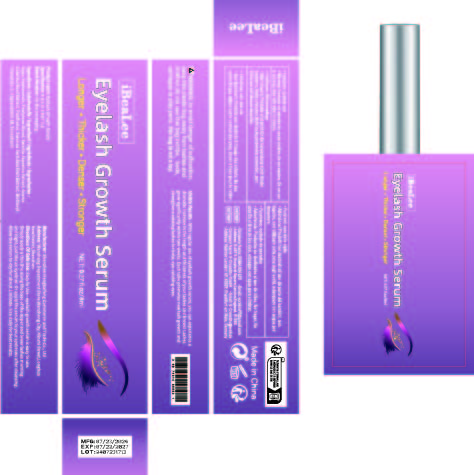 DRUG LABEL: Eyelash Growth Serum
NDC: 84117-015 | Form: LIQUID
Manufacturer: Shenzhen Hengkaifeng Commerce and Trade Co., Ltd
Category: otc | Type: HUMAN OTC DRUG LABEL
Date: 20240802

ACTIVE INGREDIENTS: PANTHENOL 1 g/100 mL
INACTIVE INGREDIENTS: WATER; HYALURONIC ACID; PENTYLENE GLYCOL; SWERTIA JAPONICA WHOLE FLOWERING; ACORUS CALAMUS ROOT; SAW PALMETTO; BIOTINOYL TRIPEPTIDE-1; OLIGOPEPTIDE-10; TOCOPHEROL

Active ingredients

Panthenol ≤1%

PURPOSE

Eyelash Growth

Uses

With regular use of eyelash growth serum, you can experience a
dramatic increase in the length and thickness of your lashes and brows! Lashes
grow significantly within two weeks. Each tube promotes new lash growth and
strengthens existing lashes for bold, eye-catching eyes.

Warnings

For external use only, Productis not intended for use by children, Do not swallow, Do not use
in eye area, rinse with water to remove.

Stop use and ask a doctor if

rash occur

Do not use

on damaged or broken skin

When using this product

Easy to Use - eyelash growth serum is easy to use.
Simply apply a thin line along the base of the upper and lower lashes morning
and night, just like an eyeliner. Or apply the serum to your eyebrows after cleansing.
Allow the serum to dry for about 1 minute. Use daily for best results.

Keep out of reach of children.

If swallwed, get medical help or contact a Poison Control Center right away.

inactive ingredients

Aqua, Hyaluronate, Pentylene Glycol, Swertia Japonica Extract, Acorus
Calamus Root Extract, Serenoa Serrulata Fruit Extract, Biotinoyl
Tripeptide-1, Oligopeptide-10, Tocopherol

DOSAGE & ADMINISTRATION

shake well before use.Wash and thoroughly dry the affectedarea. Apply 1-2 drops and gently rubinto affected area three times per day.